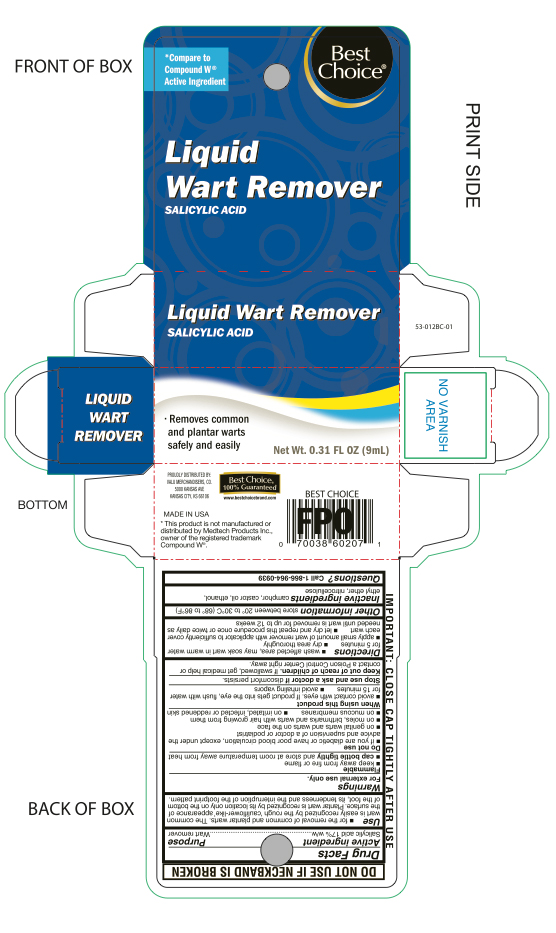 DRUG LABEL: Salicylic Acid
NDC: 63941-545 | Form: LIQUID
Manufacturer: VALU MERCHANDISERS, CO
Category: otc | Type: HUMAN OTC DRUG LABEL
Date: 20251124

ACTIVE INGREDIENTS: SALICYLIC ACID 0.17 g/9 mL
INACTIVE INGREDIENTS: PYROXYLIN; CAMPHOR (NATURAL); CASTOR OIL

Best Choice Liquid Wart Remover

Active ingredient

Salicylic acid 17%w/w

Purpose

Wart Remover

Uses

- for the removal of common and plantar warts. The common wart is easily recognized by the rough 'cauliflower-like' appearance of the surface. Plantar wart is recognized by the location only on the bottom of the foot, its tenderness and the interruption of the footprint pattern.

Warnings

For external use only.

Flammable

- keep away from fire or flame
- cap bottle tightly and store at room temerature away from heat

Do not use

- if you are a diabetic or have poor blood circulation, except under the advice and supervision of a doctor or podiatrist
- on genital warts and warts on the face
- on moles, birthmarks and warts with hair growing from them
- on mucous membranes
- on irritated, infected or reddened skin

When using this product

- avoid contact with eyes. If product gets into the eyes, flush with water for 15 minutes
- avoid inhaling vapors

Stop use and ask doctor if

discomfort persists.

Keep out of reach of children.

if swallowed, get medical help or contact a Poison Control Center right away.

Directions

- wash affected area, may soak wart in warm water for 5 minutes
- dry area thoroughly
- apply small amount of wart remover with applicator to sufficiently cover each wart
- let dry and repeat this procedure once or twice daily until wart is removed for up to 12 weeks

Other information

store between 20° to 30°C (68° to 86°F)

Inactive ingredients

camphor, castor oil, ethanol, ethyl ether, nitrocellulose

Questions?

Call 1-866-964-0939

Principal Display Panel

Best Choice

Liquid

Wart Remover

Salicylic Acid

- Removes common & plantar warts safely and easily

Net Wt 0.31 FL OZ (9mL)